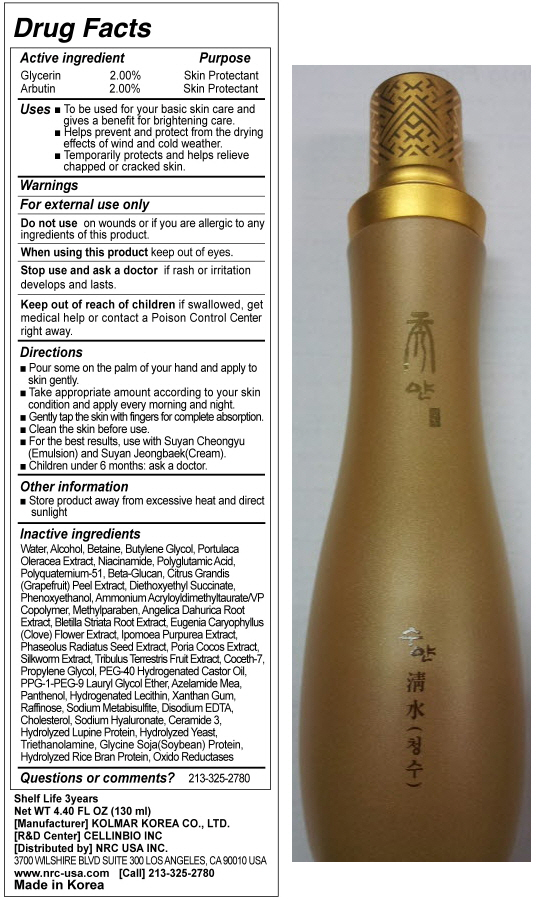 DRUG LABEL: SUYAN CHUNGSOO
NDC: 76173-1005 | Form: LIQUID
Manufacturer: Cellinbio Co Ltd
Category: otc | Type: HUMAN OTC DRUG LABEL
Date: 20111007

ACTIVE INGREDIENTS: ARBUTIN 0.26 mL/130 mL; GLYCERIN 0.26 mL/130 mL
INACTIVE INGREDIENTS: WATER; ALCOHOL; BETAINE; BUTYLENE GLYCOL; PORTULACA OLERACEA WHOLE; NIACINAMIDE; CITRUS MAXIMA FRUIT RIND; PHENOXYETHANOL; METHYLPARABEN; ANGELICA DAHURICA ROOT; BLETILLA STRIATA BULB; CLOVE; IPOMOEA PURPUREA TOP; MUNG BEAN; FU LING; TRIBULUS TERRESTRIS FRUIT; PROPYLENE GLYCOL; POLYOXYL 40 HYDROGENATED CASTOR OIL; PANTHENOL; HYDROGENATED SOYBEAN LECITHIN; XANTHAN GUM; RAFFINOSE; SODIUM METABISULFITE; EDETATE DISODIUM; CHOLESTEROL; HYALURONATE SODIUM; CERAMIDE 3; YEAST; TROLAMINE; SOY PROTEIN; RICE BRAN

SUYAN CHUNGSOO

Drug Facts

Active Ingrdient
Glycerin 2.00%
Arbutin 2.00%

Purpose

Skin Protectant

Keep out of Reach of Children

If swallowed, get medical help or contact a Posion Control Center right away.

Indication & Usage

Directions
■ Pour some on the palm of your hand and apply to skin gently.
■ Take appropriate amount according to your skin condition and apply every morning and night.
■ Gently tap the skin with fingers for complete absorption.
■ Clean the skin before use.
■ For the best results, use with Suyan Cheongyu(Emulsion) and Suyan Jeongbaek(Cream).
■ Children under 6 months: ask a doctor.

Warnings

For external use only
Do not use on wounds or if you are allergic to any ingredients of this product.
When using this product keep out of eyes.
Stop use and ask a doctor if rash or irritation develops and lasts.

Dosage & Administration

■ To be used for your basic skin care and gives a benefit for brightening care.
■ Helps prevent and protect from the drying effects of wind and cold weather.
■ Temporarily protects and helps relieve chapped or cracked skin.

Inactive Ingredient

Water, Alcohol, Betaine, Butylene Glycol, Portulaca Oleracea Extract, Niacinamide, Polyglutamic Acid, Polyquaternium-51, Beta-Glucan, Citrus Grandis(Grapefruit) Peel Extract, Diethoxyethyl Succinate, Phenoxyethanol, Ammonium Acryloyldimethyltaurate/VP Copolymer, Methylparaben, Angelica Dahurica Root Extract, Bletilla Striata Root Extract, Eugenia Caryophyllus(Clove) Flower Extract, Ipomoea Purpurea Extract, Phaseolus Radiatus Seed Extract, Poria Cocos Extract, Silkworm Extract, Tribulus Terrestris Fruit Extract, Coceth-7, Propylene Glycol, PEG-40 Hydrogenated Castor Oil, PPG-1-PEG-9 Lauryl Glycol Ether, Azelamide Mea, Panthenol, Hydrogenated Lecithin, Xanthan Gum, Raffinose, Sodium Metabisulfite, Disodium EDTA, Cholesterol, Sodium Hyaluronate, Ceramide 3, Hydrolyzed Lupine Protein, Hydrolyzed Yeast, Triethanolamine, Glycine Soja(Soybean) Protein, Hydrolyzed Rice Bran Protein, Oxido Reductases

SUYAN CHUNGSOO

SUYAN CHEONGSOO
Net WT. 4.40 FL OZ(130ml)